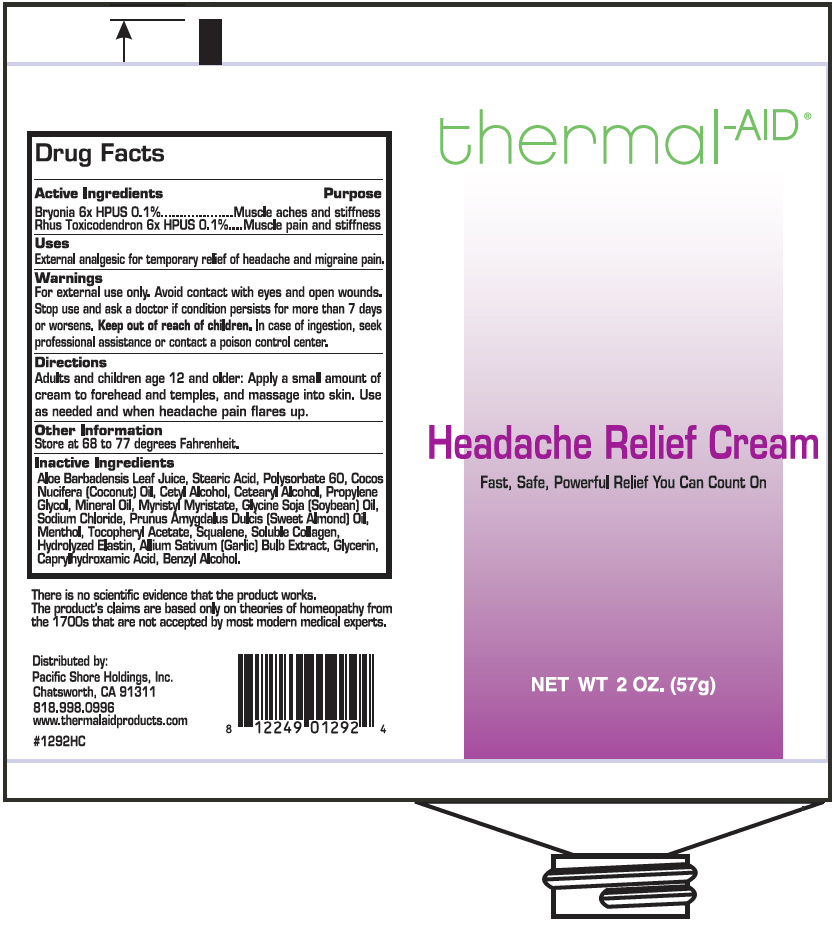 DRUG LABEL: thermal-AID 
NDC: 69314-201 | Form: CREAM
Manufacturer: Pacific Shore Holdings, Inc.
Category: homeopathic | Type: HUMAN OTC DRUG LABEL
Date: 20190830

ACTIVE INGREDIENTS: BRYONIA ALBA ROOT 6 [hp_X]/57 g; TOXICODENDRON PUBESCENS LEAF 6 [hp_X]/57 g
INACTIVE INGREDIENTS: ALOE VERA LEAF; STEARIC ACID; POLYSORBATE 60; COCONUT OIL; CETYL ALCOHOL; CETOSTEARYL ALCOHOL; PROPYLENE GLYCOL; MINERAL OIL; MYRISTYL MYRISTATE; SOYBEAN OIL; SODIUM CHLORIDE; ALMOND OIL; MENTHOL, UNSPECIFIED FORM; .ALPHA.-TOCOPHEROL ACETATE; SQUALENE; HYDROLYZED BOVINE ELASTIN (BASE; 1000 MW); GARLIC; GLYCERIN; CAPRYLHYDROXAMIC ACID; BENZYL ALCOHOL; BOVINE TYPE I COLLAGEN

thermal-AID®
Headache Relief

Drug Facts

ACTIVE INGREDIENT

Active Ingredients | Purpose
Bryonia 6x HPUS 0.1% | Muscle aches and stiffness
Rhus Toxicodendron 6x HPUS 0.1% | Muscle pain and stiffness

Uses

External analgesic for temporary relief of headache and migraine pain.

Warnings

For external use only. Avoid contact with eyes and open wounds.

Stop use and ask a doctor if condition persists for more than 7 days or worsens.

Keep out of reach of children. In case of ingestion, seek professional assistance or contact a poison control center.

Directions

Adults and children age 12 and older: Apply a small amount of cream to forehead and temples, and massage into skin. Use as needed and when headache pain flares up.

Other Information

Store at 68 to 77 degrees Fahrenheit.

Inactive Ingredients

Aloe Barbadensis Leaf Juice, Steric Acid, Polysorbate 60, Cocos Nucifera (Coconut) Oil, Cetyl Alcohol, Cetearyl Alcohol, Propylene Glycol, Mineral Oil, Myristyl Myristate, Glycine Soja (Soybean) Oil, Sodium Chloride, Prunus Amygdalus Dulcis (Sweet Almond) Oil, Menthol, Tocopheryl Acetate, Squalene, Soluble Collagen, Hydrolyzed Elastin, Allium Sativum (Garlic) Bulb Extract, Glycerin, Caprylhydroxamic Acid, Benzyl Alcohol.

Distributed by:
Pacific Shore Holdings, Inc.
Chatsworth, CA 91311

PRINCIPAL DISPLAY PANEL - 57 g Tube Label

thermal-AID®

Headache Relief Cream
Fast, Safe, Powerful Relief You Can Count On

NET WT 2 OZ. (57g)